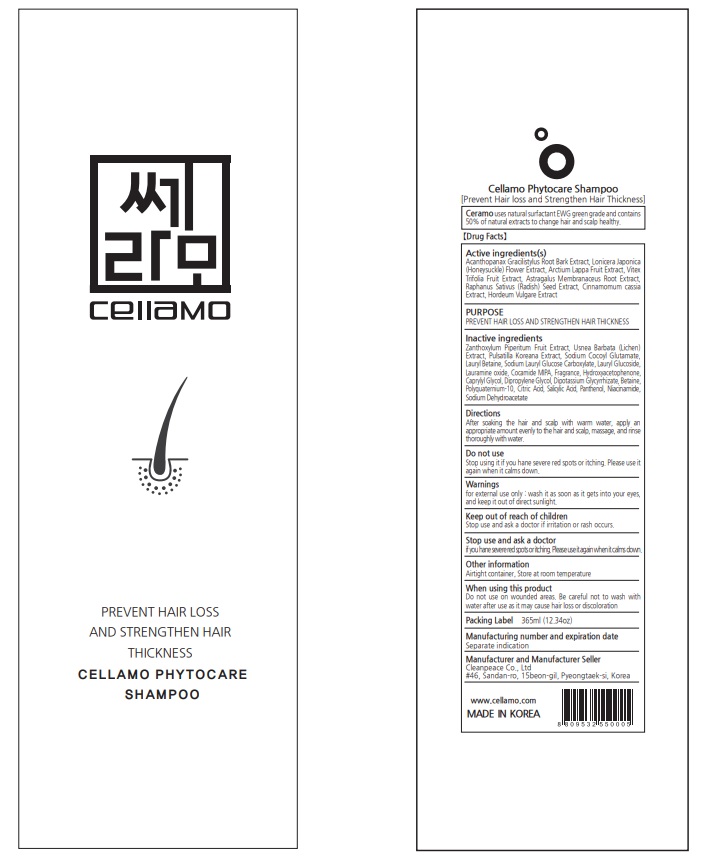 DRUG LABEL: Cellamo phytocareShampoo
NDC: 77818-302 | Form: SHAMPOO
Manufacturer: Cleanpeace Co., Ltd
Category: otc | Type: HUMAN OTC DRUG LABEL
Date: 20221216

ACTIVE INGREDIENTS: LONICERA JAPONICA FLOWER 6.1875 g/100 mL; ELEUTHEROCOCCUS NODIFLORUS ROOT BARK 6.1875 g/100 mL; VITEX TRIFOLIA FRUIT 6.1875 g/100 mL; ASTRAGALUS PROPINQUUS ROOT 6.1875 g/100 mL; RAPHANUS SATIVUS VAR. SATIVUS SEED 6.1875 g/100 mL; CHINESE CINNAMON 6.1875 g/100 mL; HORDEUM VULGARE WHOLE 6.1875 g/100 mL; ARCTIUM LAPPA FRUIT 6.1875 g/100 mL
INACTIVE INGREDIENTS: PANTHENOL 0.2 mL/100 mL; PULSATILLA KOREANA ROOT; USNEA BARBATA; SODIUM COCOYL GLUTAMATE; LAURYL BETAINE; LAURAMINE OXIDE; CAPRYLYL GLYCOL; DIPROPYLENE GLYCOL; GLYCYRRHIZINATE DIPOTASSIUM; ZANTHOXYLUM PIPERITUM FRUIT PULP; LAURYL GLUCOSIDE; COCO MONOISOPROPANOLAMIDE; HYDROXYACETOPHENONE; BETAINE; CITRIC ACID MONOHYDRATE; SODIUM DEHYDROACETATE; SALICYLIC ACID; NIACINAMIDE

Active ingredients

Acanthopanax Gracilistylus Root Bark Extract, Lonicera Japonica (Honeysuckle) Flower Extract, Arctium Lappa Fruit Extract, Vitex Trifolia Fruit Extract, Astragalus Membranaceus Root Extract, Raphanus Sativus (Radish) Seed Extract, Cinnamomum cassia Extract, Hordeum Vulgare Extract

PURPOSE

PREVENT HAIR LOSS AND STRENGTHEN HAIR THICKNESS

Inactive ingredients

Zanthoxylum Piperitum Fruit Extract, Usnea Barbata (Lichen) Extract, Pulsatilla Koreana Extract, Sodium Cocoyl Glutamate, Lauryl Betaine, Sodium Lauryl Glucose Carboxylate, Lauryl Glucoside, Lauramine oxide, Cocamide MIPA, Fragrance, Hydroxyacetophenone, Caprylyl Glycol, Dipropylene Glycol, Dipotassium Glycyrrhizate, Betaine, Polyquaternium-10, Citric Acid, Salicylic Acid, Panthenol, Niacinamide, Sodium Dehydroacetate

Directions

After soaking the hair and scalp with warm water, apply an appropriate amount evenly to the hair and scalp, massage, and rinse thoroughly with water .

Do not use

Stop using it if you hane severe red spots or itching. Please use it again when it calms down .

Warnings

for external use only : wash it as soon as it gets into your eyes, and keep it out of direct sunlight.

Keep out of reach of children. Stop use and ask a doctor if irritation or rash occurs.

Stop use and ask a doctor

if you hane severe red spots or itching. Please use it again when it calms down.

When using this product

Do not use on wounded areas. Be careful not to wash with water after use as it may cause hair loss or discoloration

Other information

Airtight container, Store at room temperature

Label

77818-302-01